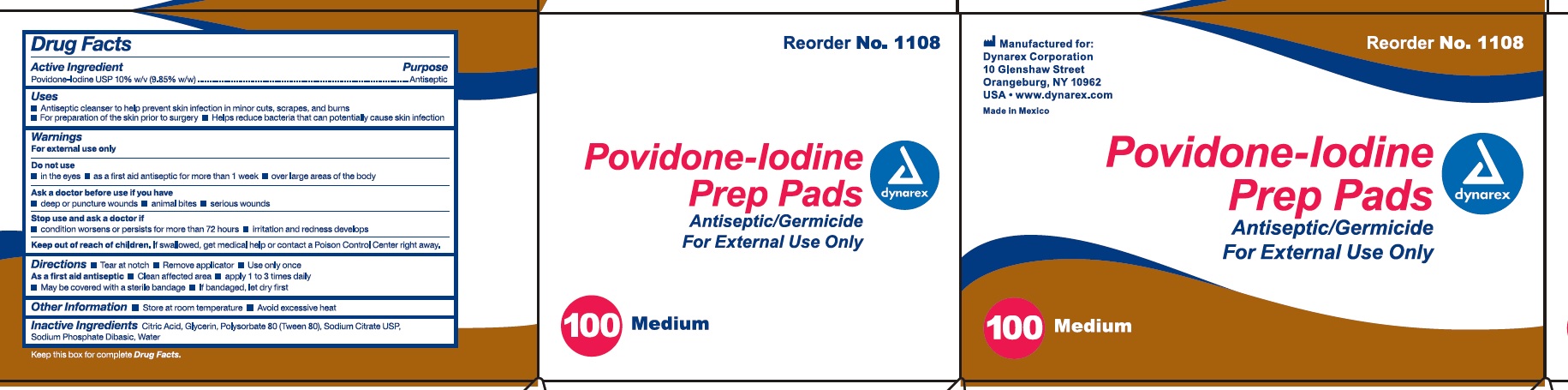 DRUG LABEL: povidine iodine
NDC: 67777-420 | Form: SWAB
Manufacturer: Dynarex Corporation
Category: otc | Type: HUMAN OTC DRUG LABEL
Date: 20221212

ACTIVE INGREDIENTS: POVIDONE-IODINE 10 g/100 g
INACTIVE INGREDIENTS: CITRIC ACID ACETATE; GLYCERIN; POLYSORBATE 80; SODIUM CITRATE; SODIUM PHOSPHATE, DIBASIC, ANHYDROUS; WATER

Povidone Iodine Prep Pad

Active Ingredient

Povidone Iodine 10% w/v (9.85% w/w)

Purpose

Antiseptic

Uses

- Antiseptic cleanser to help prevent skin infection in minor cuts, scrapes and burns.
- For preparation of the skin prior to surgery.
- Helps reduce bacteria that can potentially cause skin infections.

Warnings

For external use only

Do not use

- in the eyes.
- as a first aid antiseptic for more than 1 week.
- over large areas of the body.

Ask a doctor before use if you have:

- deep or puncture wounds
- animal bites
- serious burns

Stop use and ask a doctor if

- condition worsens or persists for more than 72 hours
- Irritation and redness develop

Keep out of reach of children

If swallowed, get medical help or contact a Poison Control Center right away

Directions:

- Tear at notch
- Remove applicator
- Use only once.

As a first aid antiseptic

- clean affected area
- apply 1 to 3 times daily
- may be covered with a sterile bandage
- If bandaged, let dry first.

Other information:

- Store at room temperature.
- Avoid excessive heat

Inactive ingredients

Citric acid, Glycerin, Polysorbate 80 (Tween 80), Sodium Citrate USP, Sodium Phosphate Dibasic, Water

Principal Display Panel

Reorder No. 1108

Povidone - Iodine Prep Pads

Antiseptic/Germicide

For External Use Only

dynarex

100 Medium